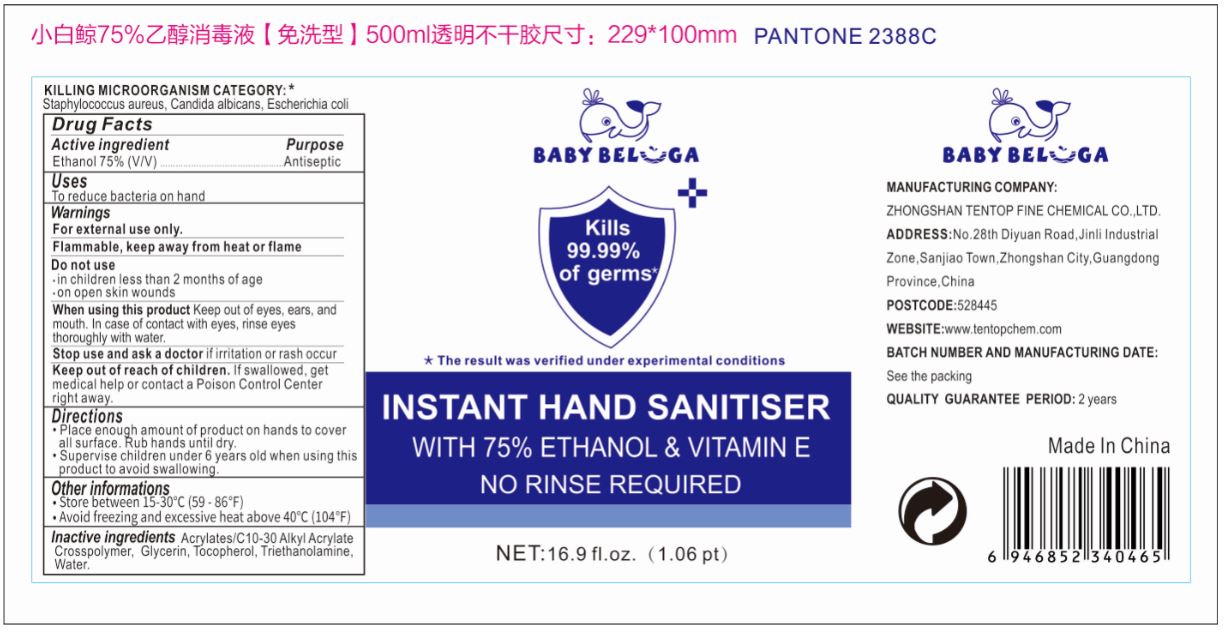 DRUG LABEL: Baby Beluga Instant Hand Sanitizer
NDC: 79425-500 | Form: GEL
Manufacturer: Zhongshan Tentop Fine Chemical Co., Ltd.
Category: otc | Type: HUMAN OTC DRUG LABEL
Date: 20200716

ACTIVE INGREDIENTS: ALCOHOL 75 mL/100 mL
INACTIVE INGREDIENTS: CARBOMER INTERPOLYMER TYPE A (ALLYL SUCROSE CROSSLINKED); TROLAMINE; GLYCERIN; TOCOPHEROL; WATER

Active Ingredient

Ethanol 75% (V/V)

Purpose

Antiseptic

Uses

To reduce bacteria on hand

Warnings

For external use only.

Flammable, keep away from heat or flame.

Do not use

- in children less than 2 months of age
- on open skin wounds

When using this product keep out of eyes, ears, and mouth. In case of contact with eyes, rinse eyes thoroughly with water.

Stop use and ask a doctor if irritation or rash occurs.

Keep out of reach of children. If swallowed, get medical help or contact a Poison Control Center right away.

Directions

- Place enough amount of product on hands to cover all surface. Rub hands until dry.
- Supervise children under 6 years old when using this product to avoid swallowing.

Other Information

- Store between 15-30°C (59-86°F).
- Avoid freezing and excessive heat above 40°C (104°F).

Inactive Ingredients

Acrylates/c10-30 alkyl acrylate crosspolymer, Glycerin, Tocopherol, Triethanolamine, Water.

Package Label/Principal Display Panel

NDC 79425-500-01; 500 ml